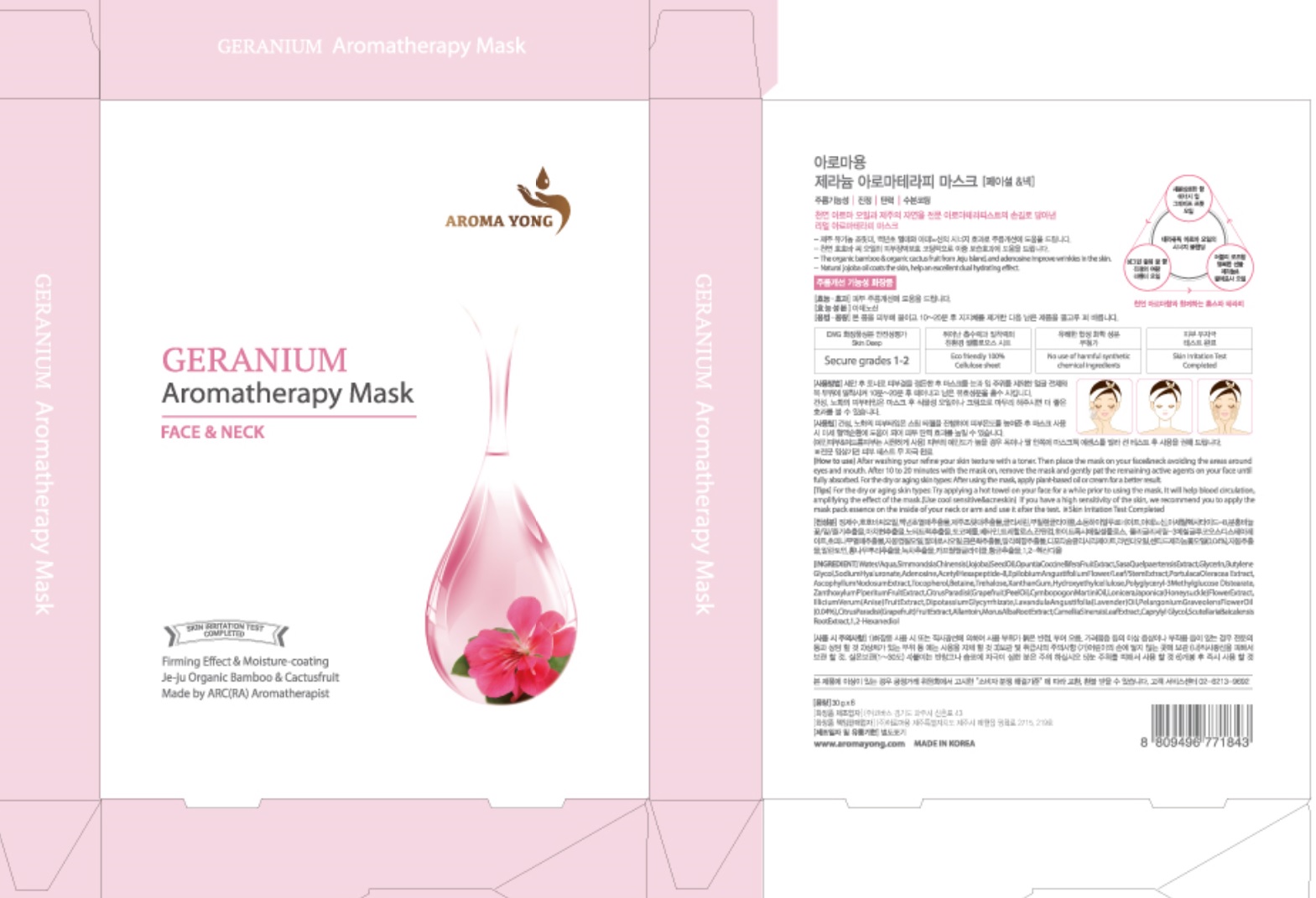 DRUG LABEL: LOVELY GERANIUM AROMATHERAPY MASK

NDC: 71392-070 | Form: PATCH
Manufacturer: AROMA YONG
Category: otc | Type: HUMAN OTC DRUG LABEL
Date: 20191203

ACTIVE INGREDIENTS: ADENOSINE 0.012 g/30 g
INACTIVE INGREDIENTS: WATER; BUTYLENE GLYCOL

71392-070

ACTIVE INGREDIENT

Active ingredients: Adenosine 0.04%

INACTIVE INGREDIENT

Inactive ingredients:

Aqua/Water, Simmondsia Chinensis Seed Oil, Sasa Quelpaertensis Extract, Opuntia Coccinellifera Fruit Extract, Glycerin, Butylene Glycol, Ascophyllum Nodosum Extract, Hydroxyethylcellulose, Epilobium Angustifolium Flower/Leaf/Stem Extract, Portulaca Oleracea Extract, Betaine, Tocopherol, Xanthan Gum, Polyglyceryl-3 Methylglucose Distearate, Trehalose, Zanthoxylum Piperitum Fruit Extract, Citrus Paradisi Peel Oil, Cymbopogon Martini Oil, Lonicera Japonica Flower Extract, Illicium Verum Fruit Extract, Lavandula Angustifolia Oil, Dipotassium Glycyrrhizate, Pelargonium Graveolens Flower Oil, Citrus Paradisi Fruit Extract, Scutellaria Baicalensis Root Extract, Allantoin, Sodium Hyaluronate, Morus Alba Root Extract, Disodium Phosphate, Polysorbate 60, Camellia Sinensis Leaf Extract, Sodium Phosphate, Caprylyl Glycol, 1,2-Hexanediol, Acetyl Hexapeptide-8, Limonene**, Geraniol**, Linalool**, Citronellol**, Citral** ** From pure essential oil

PURPOSE

Purpose: Anti-wrinkle & Soothing

WARNINGS

1) Do not use on damaged or irritated skin and skin with dermatitis 2) Do not use immediately after dermatological treatment or cosmetic surgery .3) Do not use in case of allergy to any of the ingredients 4) For external use only. 5) Do not use directly before exposure to the sunlight 6) Discontinue use if signs of irritation or rashes appear and consult with doctor. 7) Avoid direct contact with eyes. 8) Please be careful if you are irritating to adhesive bandages or patches. 9) Store in a cool and dry place, away from direct sunlight and heath (temperature storage 1-30 degrees), keep out of the reach of children.

KEEP OUT OF REACH OF CHILDREN

Uses

Helps improve the look of wrinkles.

Jeju Organic Bamboo & Cactusfruit + blended pure essential oil (Made by ARC (RA)Aromatherapist) Skin Irritation Test Completed / Eco friendly100% Cellulose sheet

Directions

After washing your face refine your skin texture with a toner. Then place the mask on your face&neck avoiding the areas around eyes and mouth. After 10 to 20 minutes with the mask on, remove the mask and gently pat the remaining active agents on your face until fully absorbed.

For the dry or aging skin types: After using the mask, apply plant-based oil or cream for a better result.